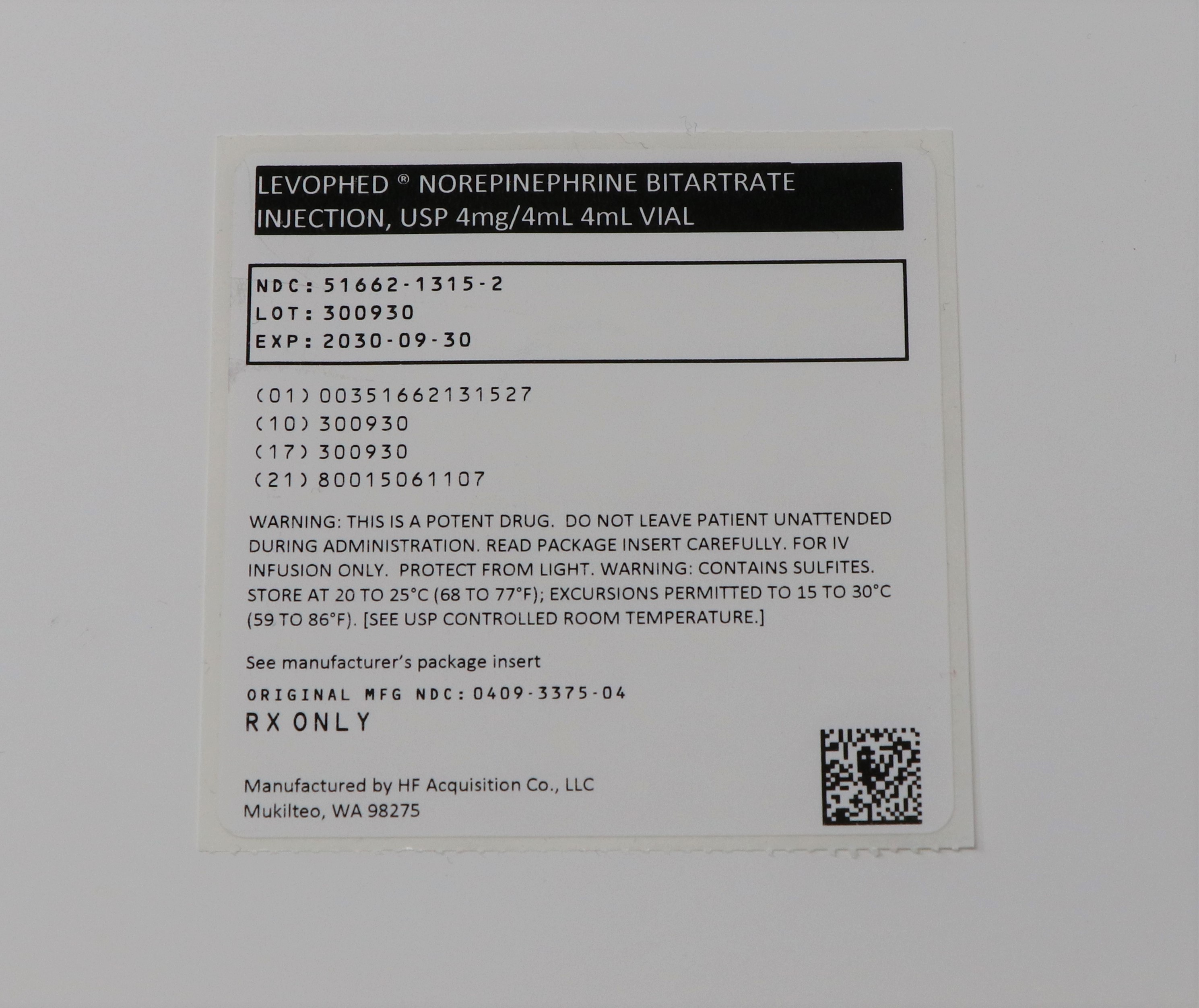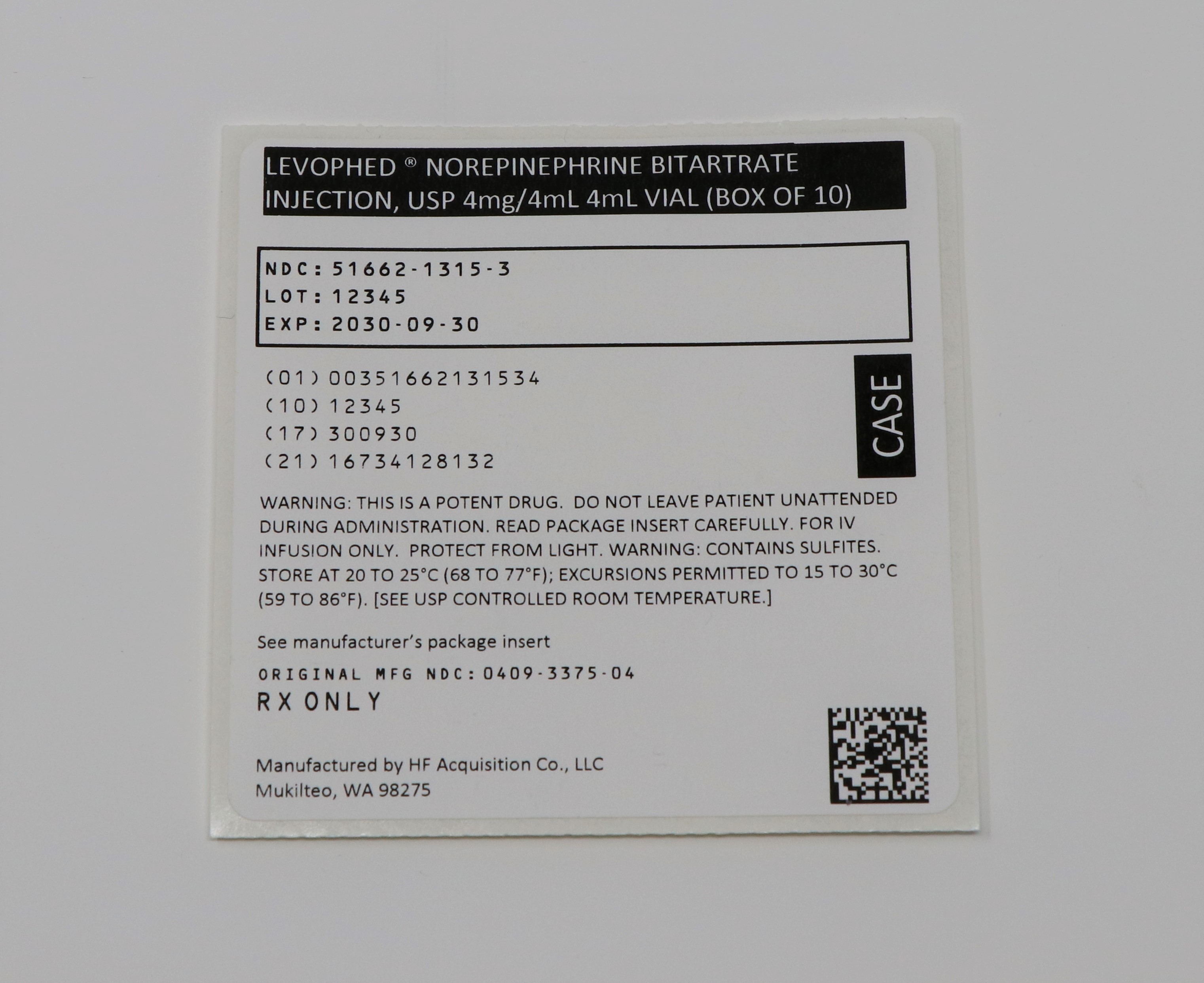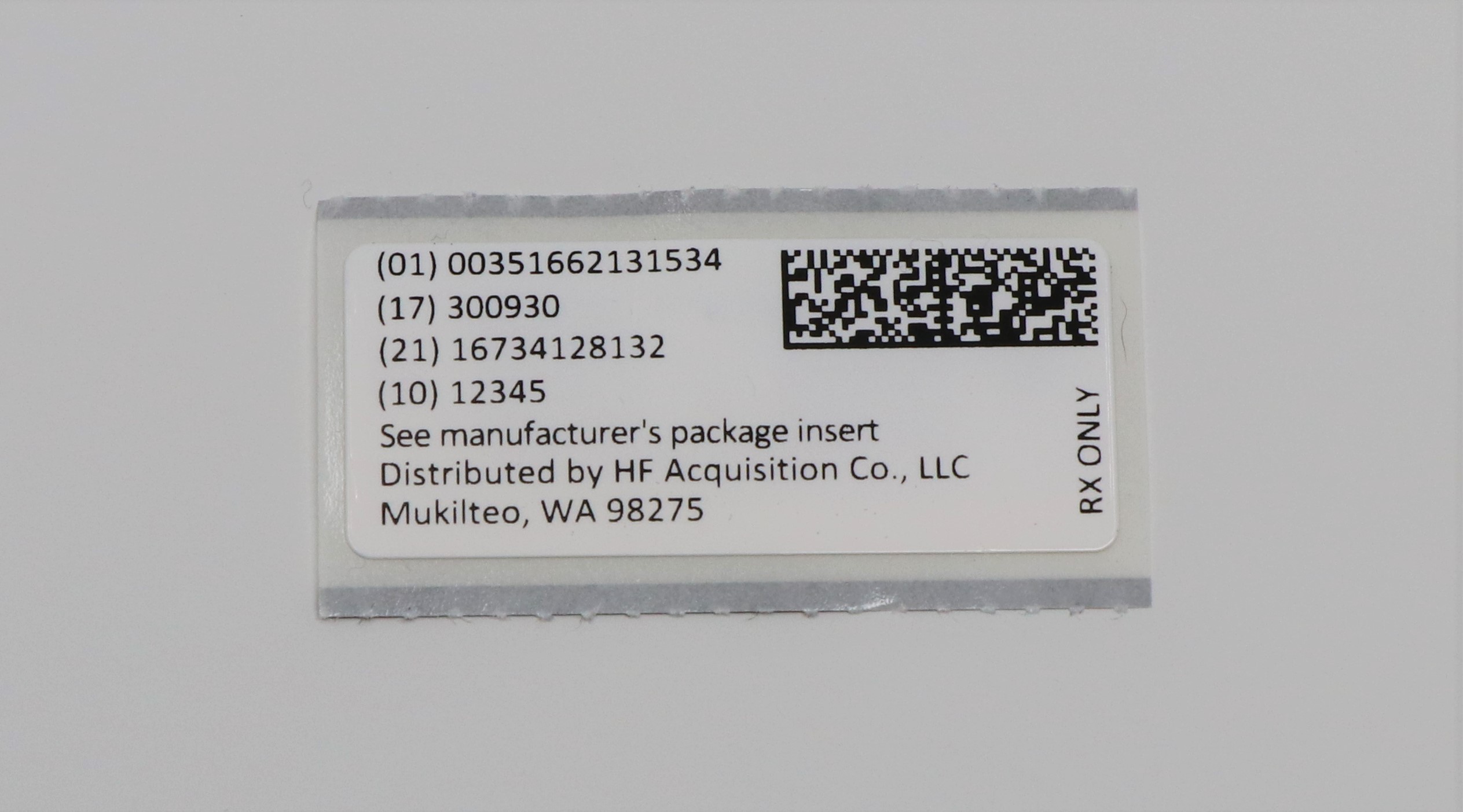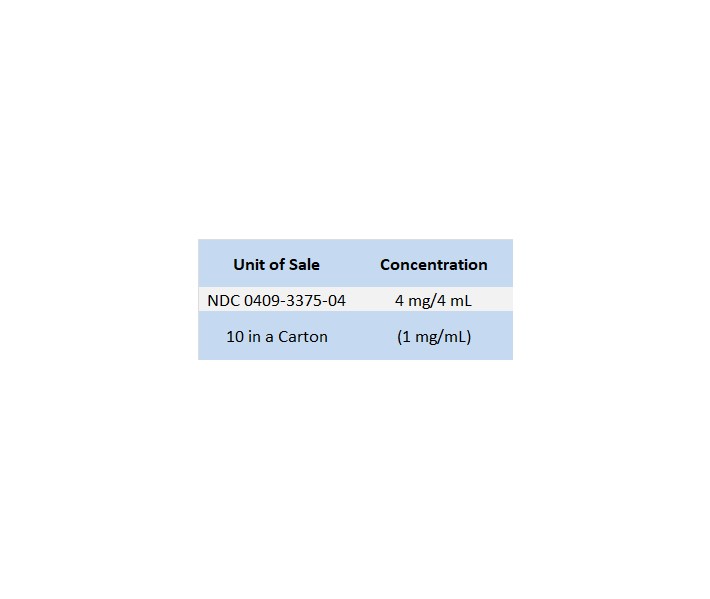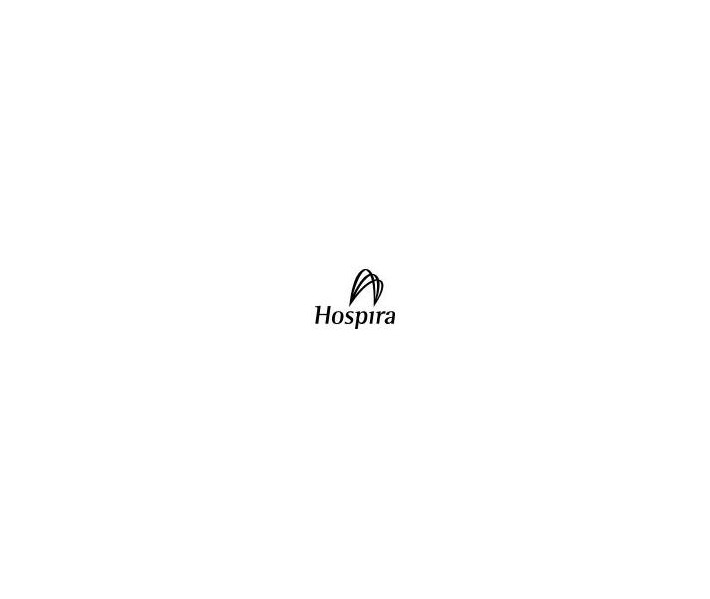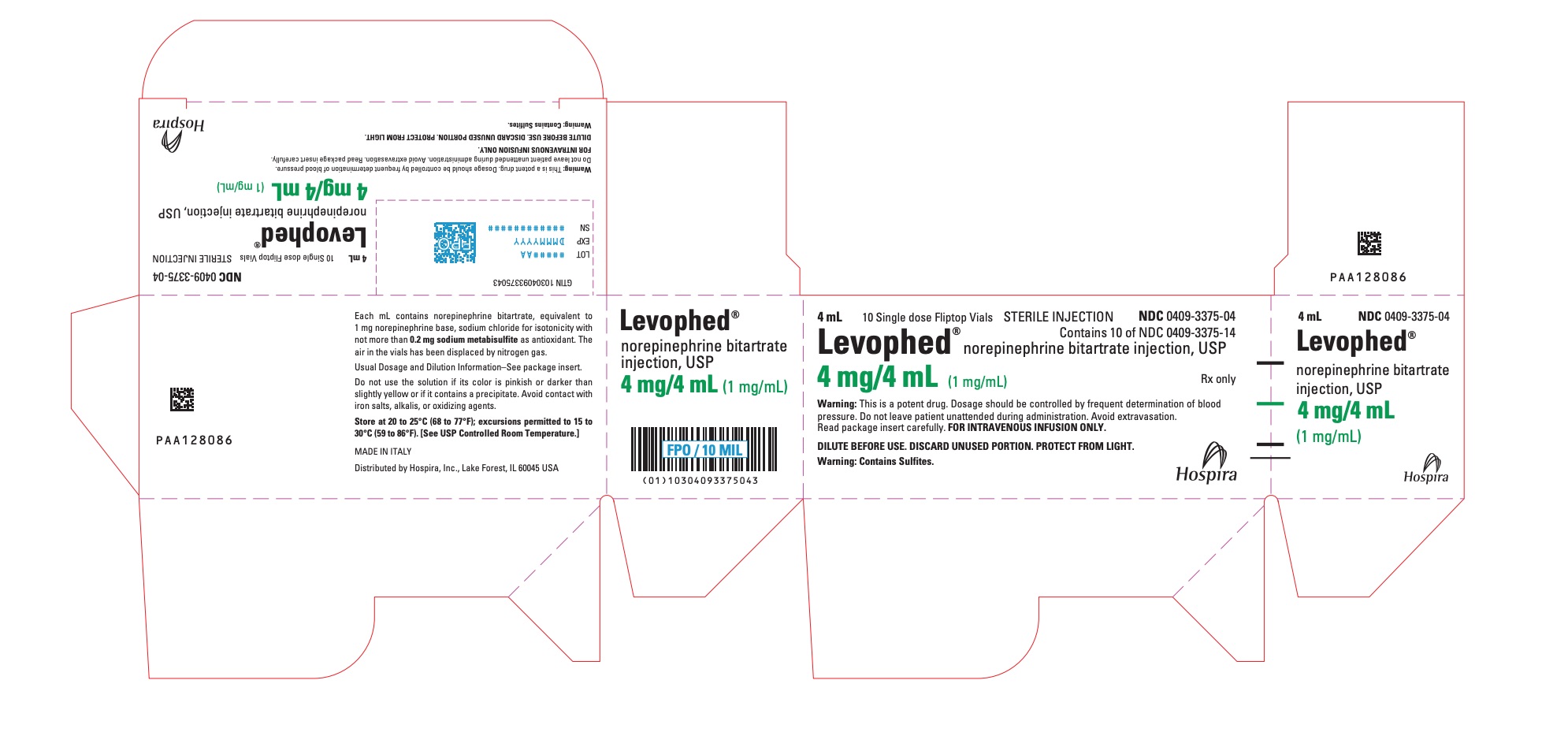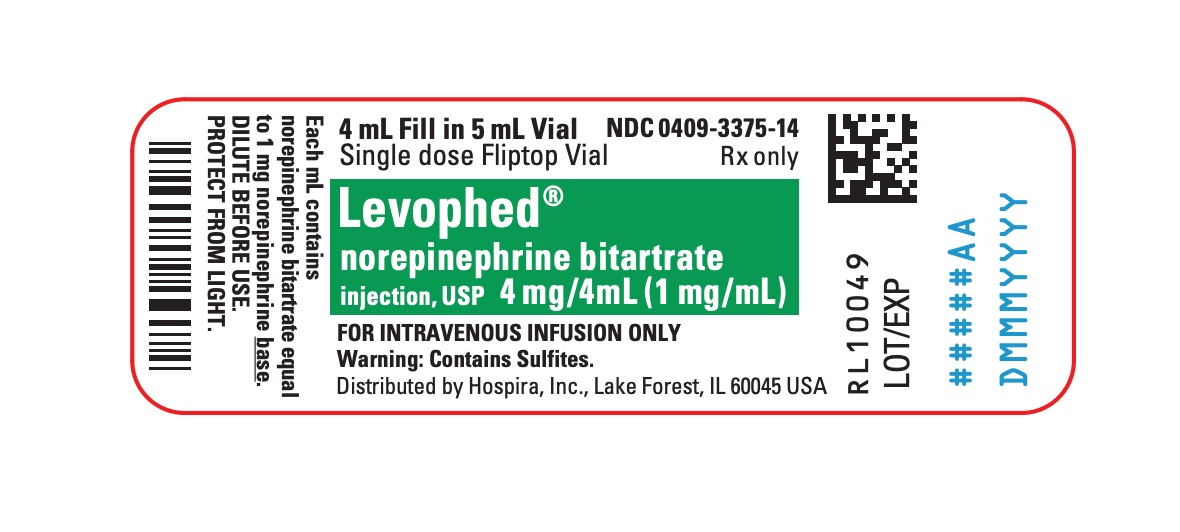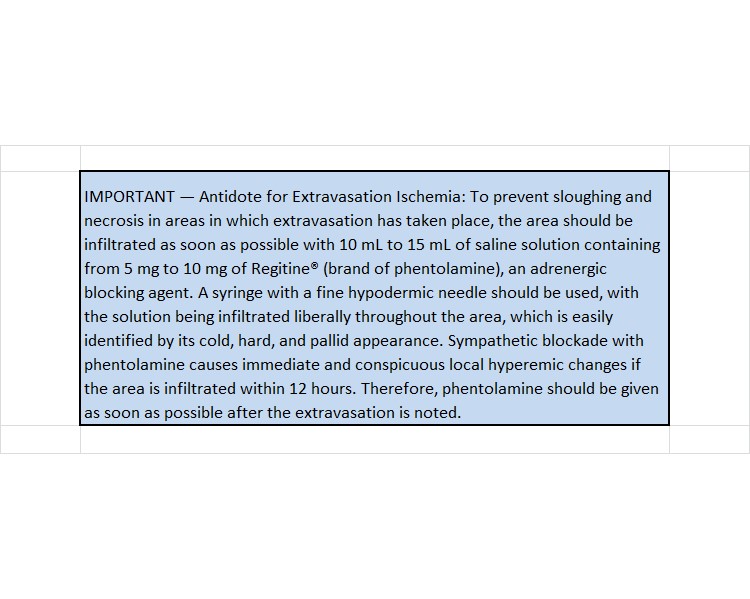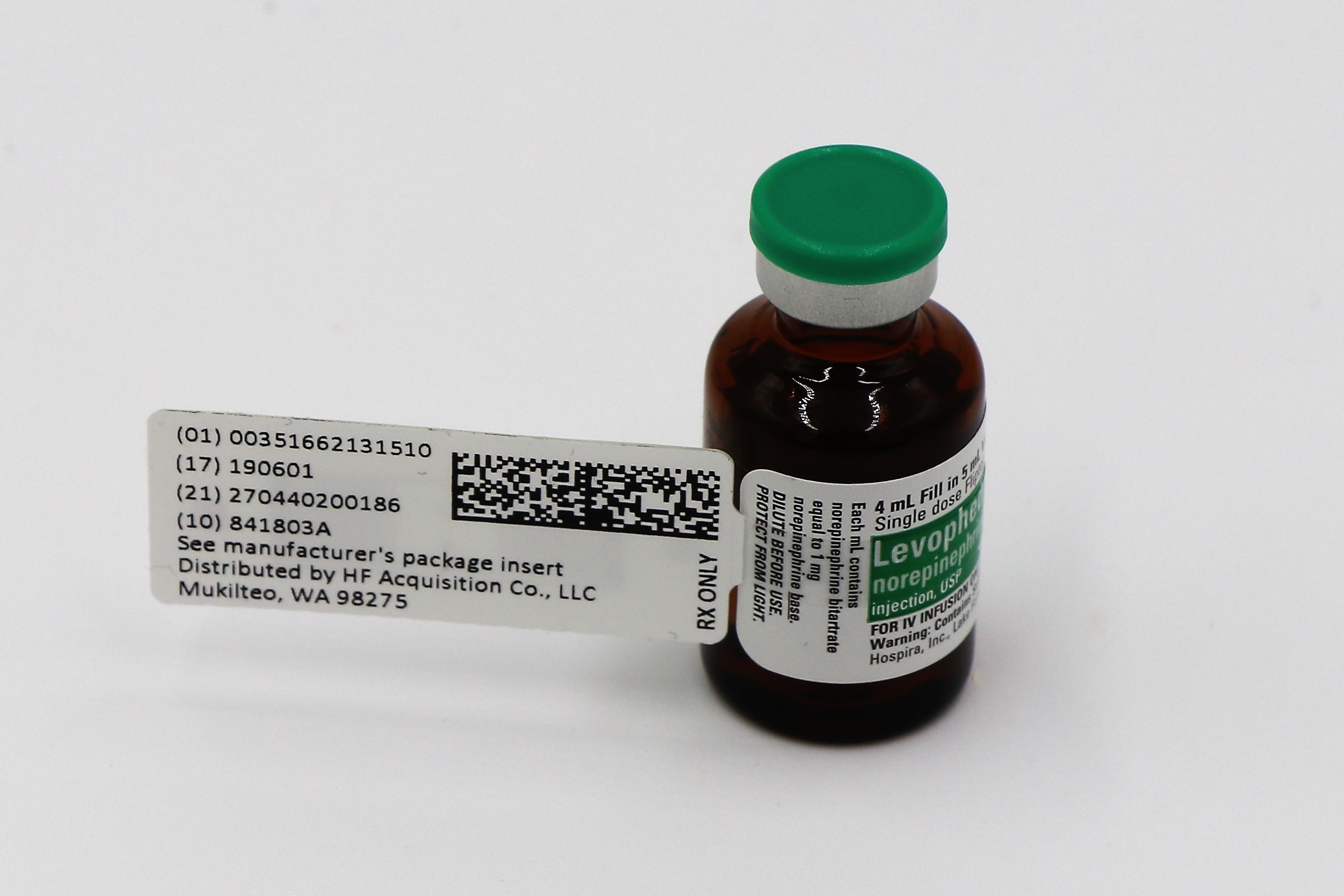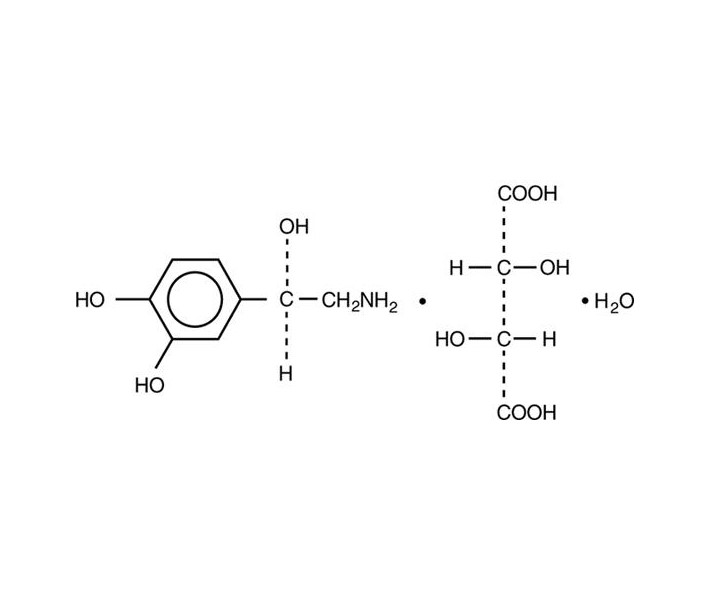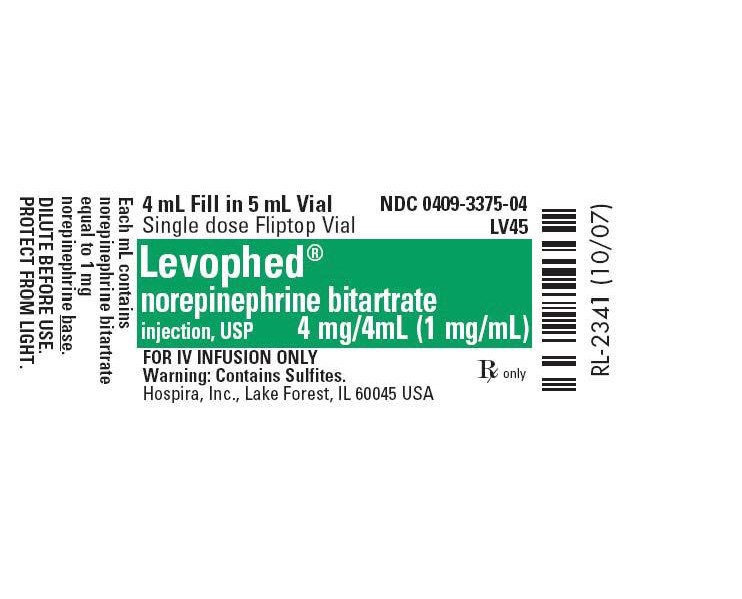 DRUG LABEL: LEVOPHED(R) NOREPINEPHRINE BITARTRATE
NDC: 51662-1315 | Form: INJECTION, SOLUTION, CONCENTRATE
Manufacturer: HF Acquisition Co LLC, DBA HealthFirst
Category: prescription | Type: HUMAN PRESCRIPTION DRUG LABEL
Date: 20210205

ACTIVE INGREDIENTS: NOREPINEPHRINE BITARTRATE 1 mg/1 mL
INACTIVE INGREDIENTS: SODIUM CHLORIDE; SODIUM METABISULFITE

LEVOPHED(R) NOREPINEPHRINE BITARTRATE INJECTION, USP 4mg/4mL 4mL VIAL

SPL UNCLASSIFIED

Norepinephrine Bitartrate

Injection, USP

Rx only

DESCRIPTION

Norepinephrine (sometimes referred to as l-arterenol/Levarterenol or l-norepinephrine) is a sympathomimetic amine which differs from epinephrine by the absence of a methyl group on the nitrogen atom.

Norepinephrine Bitartrate is (-)-α-(aminomethyl)-3,4-dihydroxybenzyl alcohol tartrate (1:1) (salt) monohydrate and has the following structural formula:

LEVOPHED is supplied in sterile aqueous solution in the form of the bitartrate salt to be administered by intravenous infusion following dilution. Norepinephrine is sparingly soluble in water, very slightly soluble in alcohol and ether, and readily soluble in acids. Each mL contains the equivalent of 1 mg base of norepinephrine, sodium chloride for isotonicity, and not more than 0.2 mg of sodium metabisulfite as an antioxidant. It has a pH of 3 to 4.5. The air in the vials has been displaced by nitrogen gas.

CLINICAL PHARMACOLOGY

LEVOPHED functions as a peripheral vasoconstrictor (alpha-adrenergic action) and as an inotropic stimulator of the heart and dilator of coronary arteries (beta-adrenergic action).

INDICATIONS & USAGE

For blood pressure control in certain acute hypotensive states (e.g., pheochromocytomectomy, sympathectomy, poliomyelitis, spinal anesthesia, myocardial infarction, septicemia, blood transfusion, and drug reactions).

As an adjunct in the treatment of cardiac arrest and profound hypotension.

CONTRAINDICATIONS

LEVOPHED should not be given to patients who are hypotensive from blood volume deficits except as an emergency measure to maintain coronary and cerebral artery perfusion until blood volume replacement therapy can be completed. If LEVOPHED is continuously administered to maintain blood pressure in the absence of blood volume replacement, the following may occur: severe peripheral and visceral vasoconstriction, decreased renal perfusion and urine output, poor systemic blood flow despite "normal" blood pressure, tissue hypoxia, and lactate acidosis.

LEVOPHED should also not be given to patients with mesenteric or peripheral vascular thrombosis (because of the risk of increasing ischemia and extending the area of infarction) unless, in the opinion of the attending physician, the administration of LEVOPHED is necessary as a life-saving procedure.

Cyclopropane and halothane anesthetics increase cardiac autonomic irritability and therefore seem to sensitize the myocardium to the action of intravenously administered epinephrine or norepinephrine. Hence, the use of LEVOPHED during cyclopropane and halothane anesthesia is generally considered contraindicated because of the risk of producing ventricular tachycardia or fibrillation.

The same type of cardiac arrhythmias may result from the use of LEVOPHED in patients with profound hypoxia or hypercarbia.

WARNINGS

LEVOPHED should be used with extreme caution in patients receiving monoamine oxidase inhibitors (MAOI) or antidepressants of the triptyline or imipramine types, because severe, prolonged hypertension may result.

LEVOPHED Bitartrate Injection contains sodium metabisulfite, a sulfite that may cause allergic-type reactions including anaphylactic symptoms and life-threatening or less severe asthmatic episodes in certain susceptible people. The overall prevalence of sulfite sensitivity in the general population is unknown. Sulfite sensitivity is seen more frequently in asthmatic than in nonasthmatic people.

PRECAUTIONS

General

Avoid Hypertension: Because of the potency of LEVOPHED and because of varying response to pressor substances, the possibility always exists that dangerously high blood pressure may be produced with overdoses of this pressor agent. It is desirable, therefore, to record the blood pressure every two minutes from the time administration is started until the desired blood pressure is obtained, then every five minutes if administration is to be continued.

The rate of flow must be watched constantly, and the patient should never be left unattended while receiving LEVOPHED. Headache may be a symptom of hypertension due to overdosage.

Site of Infusion: Whenever possible, infusions of LEVOPHED should be given into a large vein, particularly an antecubital vein because, when administered into this vein, the risk of necrosis of the overlying skin from prolonged vasoconstriction is apparently very slight. Some authors have indicated that the femoral vein is also an acceptable route of administration. A catheter tie-in technique should be avoided, if possible, since the obstruction to blood flow around the tubing may cause stasis and increased local concentration of the drug. Occlusive vascular diseases (for example, atherosclerosis, arteriosclerosis, diabetic endarteritis, Buerger's disease) are more likely to occur in the lower than in the upper extremity. Therefore, one should avoid the veins of the leg in elderly patients or in those suffering from such disorders. Gangrene has been reported in a lower extremity when infusions of LEVOPHED were given in an ankle vein.

Extravasation: The infusion site should be checked frequently for free flow. Care should be taken to avoid extravasation of LEVOPHED into the tissues, as local necrosis might ensue due to the vasoconstrictive action of the drug. Blanching along the course of the infused vein, sometimes without obvious extravasation, has been attributed to vasa vasorum constriction with increased permeability of the vein wall, permitting some leakage.

This also may progress on rare occasions to superficial slough, particularly during infusion into leg veins in elderly patients or in those suffering from obliterative vascular disease. Hence, if blanching occurs, consideration should be given to the advisability of changing the infusion site at intervals to allow the effects of local vasoconstriction to subside.

Drug Interactions: Cyclopropane and halothane anesthetics increase cardiac autonomic irritability and therefore seem to sensitize the myocardium to the action of intravenously administered epinephrine or norepinephrine. Hence, the use of LEVOPHED during cyclopropane and halothane anesthesia is generally considered contraindicated because of the risk of producing ventricular tachycardia or fibrillation. The same type of cardiac arrhythmias may result from the use of LEVOPHED in patients with profound hypoxia or hypercarbia.

LEVOPHED should be used with extreme caution in patients receiving monoamine oxidase inhibitors (MAOI) or antidepressants of the triptyline or imipramine types, because severe, prolonged hypertension may result.

Carcinogenesis, Mutagenesis, Impairment of Fertility: Studies have not been performed.

Pregnancy: Animal reproduction studies have not been conducted with LEVOPHED. It is also not known whether LEVOPHED can cause fetal harm when administered to a pregnant woman or can affect reproduction capacity. LEVOPHED should be given to a pregnant woman only if clearly needed.

Nursing Mothers: It is not known whether this drug is excreted in human milk. Because many drugs are excreted in human milk, caution should be exercised when LEVOPHED is administered to a nursing woman.

Pediatric Use: Safety and effectiveness in pediatric patients has not been established.

Geriatric Use: Clinical studies of LEVOPHED did not include sufficient numbers of subjects aged 65 and over to determine whether they respond differently from younger subjects. Other reported clinical experience has not identified differences in responses between the elderly and younger patients. In general, dose selection for an elderly patient should be cautious, usually starting at the low end of the dosing range, reflecting the greater frequency of decreased hepatic, renal, or cardiac function, and of concomitant disease or other drug therapy.

LEVOPHED infusions should not be administered into the veins in the leg in elderly patients (see PRECAUTIONS, General).

ADVERSE REACTIONS

The following reactions can occur:

Body As A Whole: Ischemic injury due to potent vasoconstrictor action and tissue hypoxia.

Cardiovascular System: Bradycardia, probably as a reflex result of a rise in blood pressure, arrhythmias, and stress cardiomyopathy.

Nervous System: Anxiety, transient headache.

Respiratory System: Respiratory difficulty.

Skin and Appendages: Extravasation necrosis at injection site.

Prolonged administration of any potent vasopressor may result in plasma volume depletion which should be continuously corrected by appropriate fluid and electrolyte replacement therapy. If plasma volumes are not corrected, hypotension may recur when LEVOPHED is discontinued, or blood pressure may be maintained at the risk of severe peripheral and visceral vasoconstriction (e.g., decreased renal perfusion) with diminution in blood flow and tissue perfusion with subsequent tissue hypoxia and lactic acidosis and possible ischemic injury. Gangrene of extremities has been rarely reported.

Overdoses or conventional doses in hypersensitive persons (e.g., hyperthyroid patients) cause severe hypertension with violent headache, photophobia, stabbing retrosternal pain, pallor, intense sweating, and vomiting.

OVERDOSAGE

Overdosage with LEVOPHED may result in headache, severe hypertension, reflex bradycardia, marked increase in peripheral resistance, and decreased cardiac output. In case of accidental overdosage, as evidenced by excessive blood pressure elevation, discontinue LEVOPHED until the condition of the patient stabilizes.

DOSAGE & ADMINISTRATION

Norepinephrine Bitartrate Injection is a concentrated, potent drug which must be diluted in dextrose containing solutions prior to infusion. An infusion of LEVOPHED should be given into a large vein (see PRECAUTIONS).

Restoration of Blood Pressure in Acute Hypotensive States

Blood volume depletion should always be corrected as fully as possible before any vasopressor is administered. When, as an emergency measure, intraaortic pressures must be maintained to prevent cerebral or coronary artery ischemia, LEVOPHED can be administered before and concurrently with blood volume replacement.

Diluent: LEVOPHED should be diluted in 5 percent dextrose injection or 5 percent dextrose and sodium chloride injections. These dextrose containing fluids are protection against significant loss of potency due to oxidation. Administration in saline solution alone is not recommended. Whole blood or plasma, if indicated to increase blood volume, should be administered separately (for example, by use of a Y-tube and individual containers if given simultaneously).

Average Dosage: Add the content of the vial (4 mg/4 mL) of LEVOPHED to 1,000 mL of a 5 percent dextrose containing solution. Each mL of this dilution contains 4 mcg of the base of LEVOPHED. Give this solution by intravenous infusion. Insert a plastic intravenous catheter through a suitable bore needle well advanced centrally into the vein and securely fixed with adhesive tape, avoiding, if possible, a catheter tie-in technique as this promotes stasis. An IV drip chamber or other suitable metering device is essential to permit an accurate estimation of the rate of flow in drops per minute. After observing the response to an initial dose of 2 mL to 3 mL (from 8 mcg to 12 mcg of base) per minute, adjust the rate of flow to establish and maintain a low normal blood pressure (usually 80 mm Hg to 100 mm Hg systolic) sufficient to maintain the circulation to vital organs. In previously hypertensive patients, it is recommended that the blood pressure should be raised no higher than 40 mm Hg below the preexisting systolic pressure. The average maintenance dose ranges from 0.5 mL to 1 mL per minute (from 2 mcg to 4 mcg of base).

High Dosage: Great individual variation occurs in the dose required to attain and maintain an adequate blood pressure. In all cases, dosage of LEVOPHED should be titrated according to the response of the patient. Occasionally much larger or even enormous daily doses (as high as 68 mg base or 17 vials) may be necessary if the patient remains hypotensive, but occult blood volume depletion should always be suspected and corrected when present. Central venous pressure monitoring is usually helpful in detecting and treating this situation.

Fluid Intake: The degree of dilution depends on clinical fluid volume requirements. If large volumes of fluid (dextrose) are needed at a flow rate that would involve an excessive dose of the pressor agent per unit of time, a solution more dilute than 4 mcg per mL should be used. On the other hand, when large volumes of fluid are clinically undesirable, a concentration greater than 4 mcg per mL may be necessary.

Duration of Therapy: The infusion should be continued until adequate blood pressure and tissue perfusion are maintained without therapy. Infusions of LEVOPHED should be reduced gradually, avoiding abrupt withdrawal. In some of the reported cases of vascular collapse due to acute myocardial infarction, treatment was required for up to six days.

Adjunctive Treatment in Cardiac Arrest

Infusions of LEVOPHED are usually administered intravenously during cardiac resuscitation to restore and maintain an adequate blood pressure after an effective heartbeat and ventilation have been established by other means. [LEVOPHED's powerful beta-adrenergic stimulating action is also thought to increase the strength and effectiveness of systolic contractions once they occur.]

Average Dosage: To maintain systemic blood pressure during the management of cardiac arrest, LEVOPHED is used in the same manner as described under Restoration of Blood Pressure in Acute Hypotensive States.

Parenteral drug products should be inspected visually for particulate matter and discoloration prior to use, whenever solution and container permit.

Do not use the solution if its color is pinkish or darker than slightly yellow or if it contains a precipitate.

Avoid contact with iron salts, alkalis, or oxidizing agents.

HOW SUPPLIED

LEVOPHED(R) NOREPINEPHRINE BITARTRATE INJECTION, USP is supplied in the following dosage forms.

NDC 51662-1315-1

LEVOPHED(R) NOREPINEPHRINE BITARTRATE INJECTION, USP 4mg/4mL 4mL VIAL

NDC 51662-1315-2

Pouch containing a single LEVOPHED(R) NOREPINEPHRINE BITARTRATE INJECTION, USP 4mg/4mL 4mL

NDC 51662-1315-3

Case containing 10 pouches of LEVOPHED(R) NOREPINEPHRINE BITARTRATE INJECTION, USP 4mg/4mL 4mL

HF Acquisition Co LLC, DBA HealthFirst
Mukilteo, WA 98275

Also supplied in the following manufacture supplied dosage forms

LEVOPHED (norepinephrine bitartrate) injection, USP, contains the equivalent of 1 mg base of LEVOPHED per 1 mL (4 mg/4 mL).

Supplied as:

Store at 20 to 25°C (68 to 77°F); excursions permitted to 15 to 30°C (59 to 86°F). [See USP Controlled Room Temperature.]

Protect from light.

Regitine, trademark, CIBA Pharmaceuticals Company.

Distributed by Hospira, Inc., Lake Forest, IL 60045 USA

LAB-1150-3.0

Revised: 09/2018